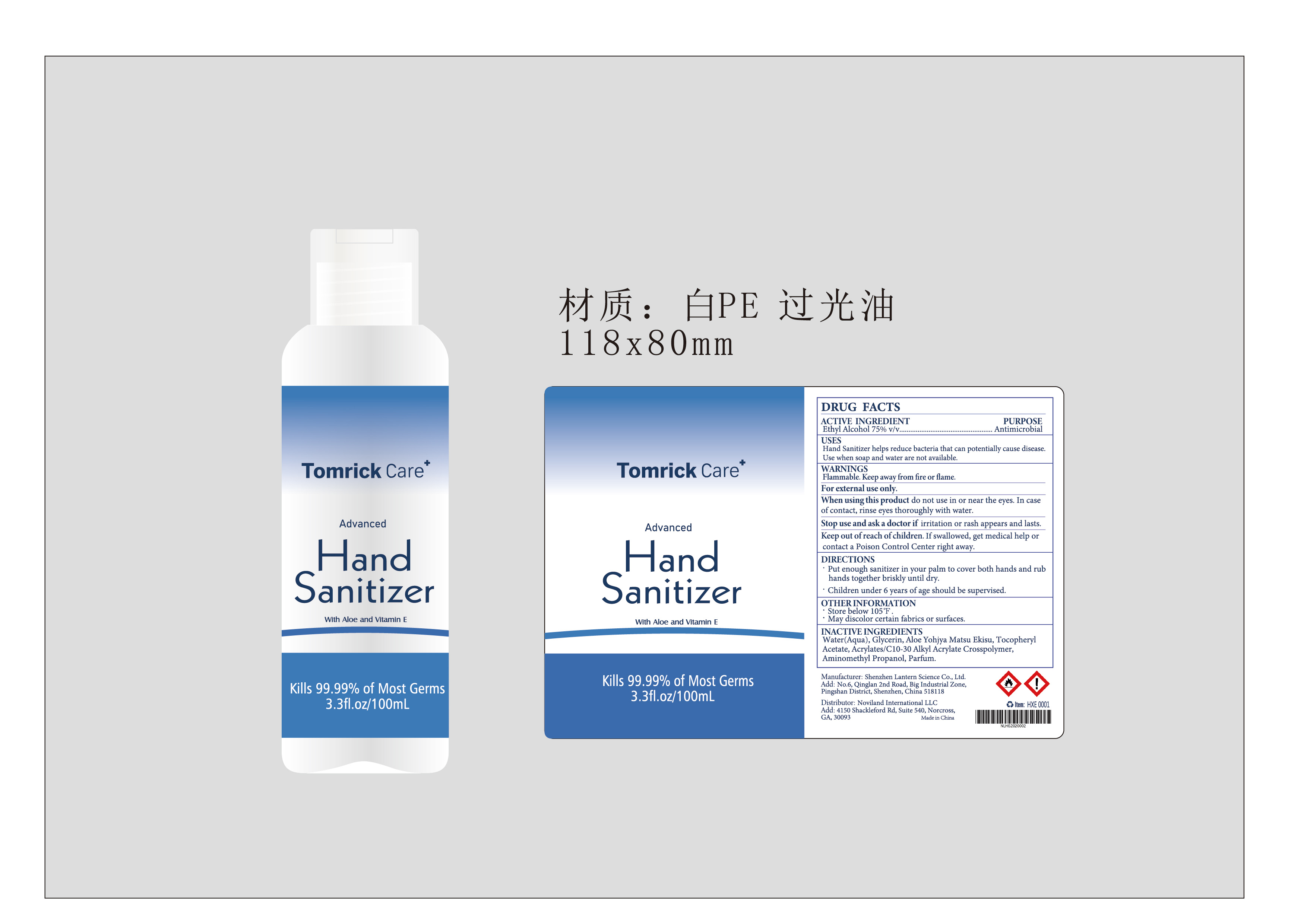 DRUG LABEL: Tomrick Care Hand sanitizer 100ml HXE0001
NDC: 54860-255 | Form: LIQUID
Manufacturer: Shenzhen Lantern Scicence Co.,Ltd.
Category: otc | Type: HUMAN OTC DRUG LABEL
Date: 20200509

ACTIVE INGREDIENTS: ALCOHOL 75 mL/100 mL
INACTIVE INGREDIENTS: .ALPHA.-TOCOPHEROL ACETATE 0.01 mL/100 mL; ALOE ANDONGENSIS WHOLE 0.01 mL/100 mL; ALOE 0.15 mL/100 mL; CARBOMER INTERPOLYMER TYPE A (55000 CPS) 0.3 mL/100 mL; AMINOMETHYLPROPANOL 0.09 mL/100 mL; WATER 23.85 mL/100 mL; GLYCERIN 0.5 mL/100 mL

Tomrick Care Hand sanitizer 100ml HXE0001

Active Ingredient

Active Ingredient Purpose

Ethyl Alcohol 75%（V/V） Antiseptic

USE

Hand sanitizer helps reduce bacteria that can potentially cause disease.Use when soap and water are not available.

DOSAGE AND ADMINISTRATION

Recommended for repeated use.

use anywhere without water.

Warning

Flammable.Keep away from fire or flame

For external use only

WARNINGS AND PRECAUTIONS

For external use only.

Flammable, keep away from heat and flame.

STOP USE

Discontinue if skin becomes irritated and ask a doctor .

Keep out of reach of children. In case of accidental ingestion, seek professional assistance or contact a poson control center immediately.

Inactive ingredients

Aqua,Glycerin,Aloe Yohjyu Matsu Ekisu,Tocopheryl Acetate,Acrylates/C10-30 Alkyl Acrylate Crosspolymer,Aminomethyl Propanol,Parfum.

Directions

Put enough sanitizer in your palm to cover both hands and rub hands together briskly until dry.

Children under 6 years of age should be supervised.

When using this product

keep out of eyes. In case of contact with eyes, flush thoroughly with water.

Do not inhale or ingest.

Avoid contact with broken skin.

Other information

Do not store above 105F.

May discolor some fabrics.

Harmful to wood finishes and plastics.

When using this product

do not use in or near the eyes.In case of contact,rinse eyes thoroughly with water.

Stop use and ask a doctor if irritation or rash appears and lasts.

Keep out of reach of children.If swallowed,get medical help or contact a poison control center right away.